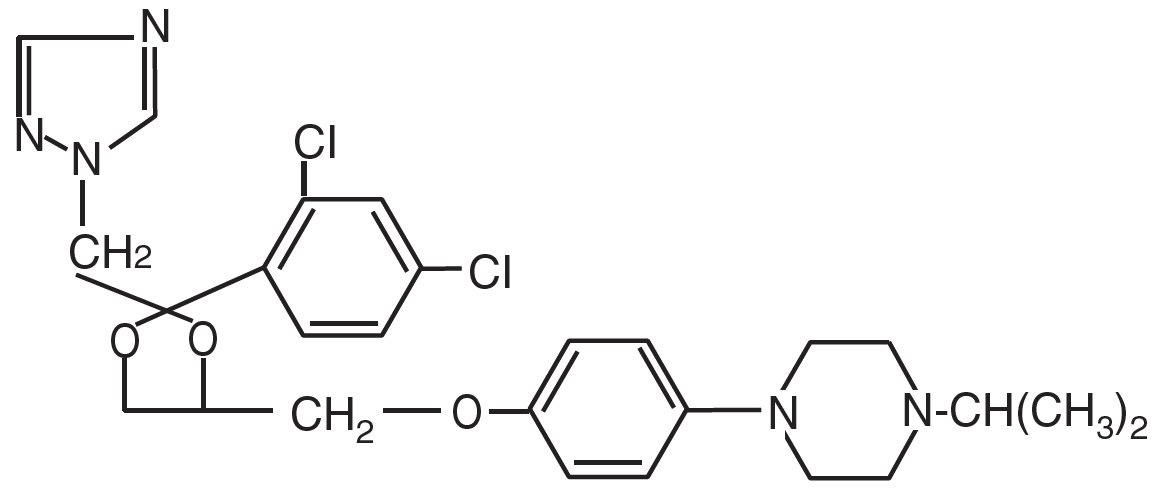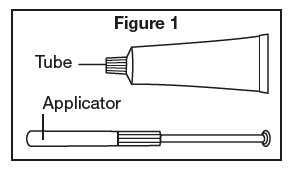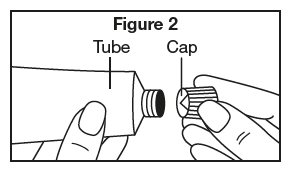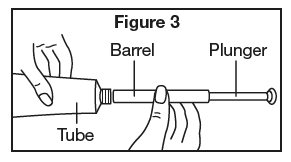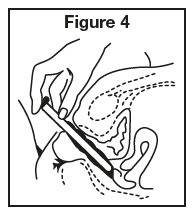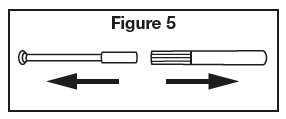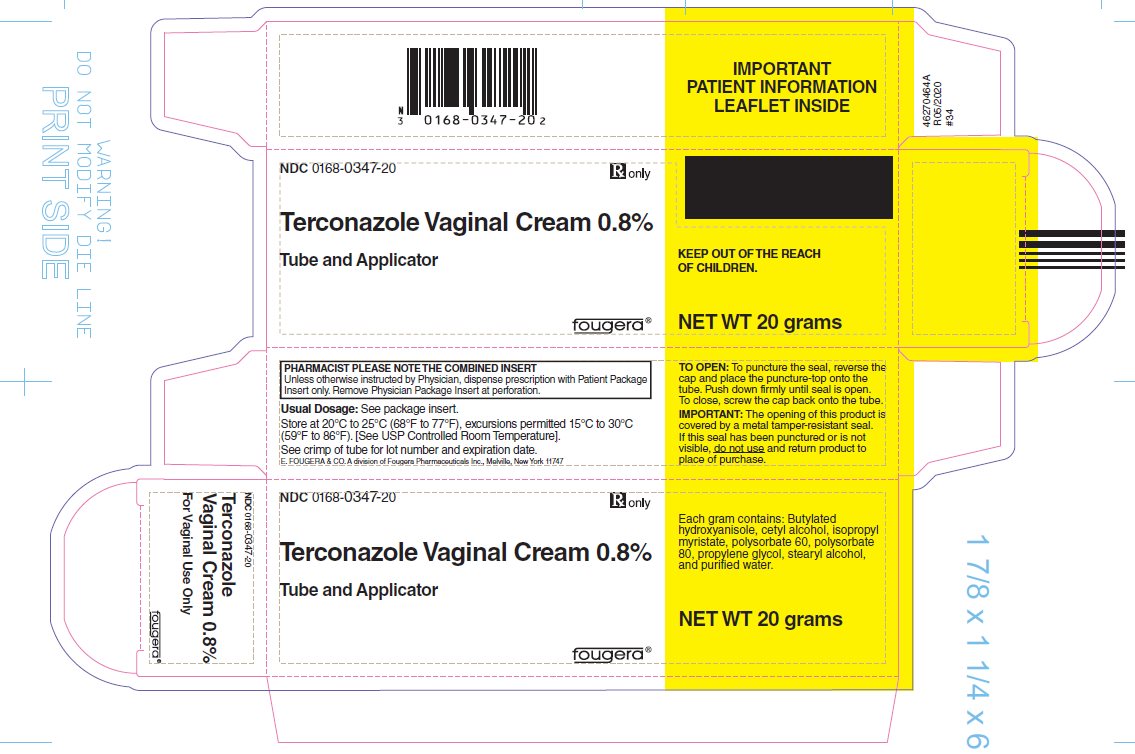 DRUG LABEL: Terconazole
NDC: 0168-0347 | Form: CREAM
Manufacturer: E. Fougera & Co. a division of Fougera Pharmaceuticals, LLC
Category: prescription | Type: HUMAN PRESCRIPTION DRUG LABEL
Date: 20260128

ACTIVE INGREDIENTS: terconazole 8 mg/1 g
INACTIVE INGREDIENTS: butylated hydroxyanisole; cetyl alcohol; isopropyl myristate; polysorbate 60; polysorbate 80; propylene glycol; stearyl alcohol; water

HIGHLIGHTS OF PRESCRIBING INFORMATION

These highlights do not include all the information needed to use TERCONAZOLE VAGINAL CREAM safely and effectively. See full prescribing information for TERCONAZOLE VAGINAL CREAM.
TERCONAZOLE vaginal cream,
Initial U.S. Approval: 1987

1 INDICATIONS AND USAGE

Terconazole Vaginal Cream is an azole antifungal indicated for the treatment of vulvovaginal candidiasis in adult females. (1)

2 DOSAGE AND ADMINISTRATION

- One full applicator (5 grams) of Terconazole Vaginal Cream administered intravaginally once daily at bedtime for three (3) consecutive days. (2)
- Not for oral or ophthalmic use. (2)

3 DOSAGE FORMS AND STRENGTHS

Vaginal cream containing terconazole 0.8%: supplied in a 20 gram tube with a measured dose applicator. Each applicator delivers 40 mg of terconazole. (3)

4 CONTRAINDICATIONS

Known hypersensitivity to terconazole or any other component of the cream (4)

5 WARNINGS AND PRECAUTIONS

Risk of Skin Irritation and Flu-Like Symptoms: Discontinue Terconazole Vaginal Cream and do not retreat if skin irritation, fever, chills or flu-like symptoms are reported during use. (5)

6 ADVERSE REACTIONS

Most common adverse reactions (incidence ≥ 2%) were headache, dysmenorrhea, genital burning and itching, and abdominal pain. (6)

To report SUSPECTED ADVERSE REACTIONS, contact Fougera at 1-800-645-9833 or FDA at 1-800-FDA-1088 or www.fda.gov/medwatch.

FULL PRESCRIBING INFORMATION

1 INDICATIONS AND USAGE

Terconazole Vaginal Cream, is indicated for the treatment of vulvovaginal candidiasis in adult females.

2 DOSAGE AND ADMINISTRATION

The recommended dose is one applicator full of Terconazole Vaginal Cream (5 grams of cream containing 40 mg terconazole) administered intravaginally once daily at bedtime for three consecutive days. Terconazole Vaginal Cream is not for oral or ophthalmic use.

3 DOSAGE FORMS AND STRENGTHS

Terconazole Vaginal Cream, 0.8% contains 8mg terconazole per gram of cream. Each measured dose applicator delivers 5 grams of cream containing 40 mg of terconazole.

4 CONTRAINDICATIONS

Terconazole Vaginal Cream, 0.8% is contraindicated in patients with known hypersensitivity to terconazole or to any of the components of the cream.

5 WARNINGS AND PRECAUTIONS

5.1 Risk of Skin Irritation and Flu-Like Symptoms

Discontinue Terconazole Vaginal Cream and do not retreat, if skin irritation, fever, chills or flu-like symptoms are reported during use.

5.2 Hypersensitivity

There is no information regarding cross-hypersensitivity between terconazole and other azole antifungal agents. Monitor patients with a history of hypersensitivity to azoles.

6 ADVERSE REACTIONS

6.1 Clinical Trial Experience

Because clinical trials are conducted under widely varying conditions, adverse reaction rates observed in clinical trials of a drug cannot be directly compared to rates in the clinical trials of another drug and may not reflect the rates observed in practice. The adverse reaction information from clinical trials does, however, provide a basis for identifying the adverse reactions that appear to be related to drug use and estimating their relative rates.

During a controlled clinical trial conducted in the United States, patients with vulvovaginal candidiasis were treated with Terconazole Vaginal Cream, 0.8% for 3 days (n=231) or Terazol®3 for 3 days (n=229) [see Clinical Studies (14)]. Table 1 lists the adverse reactions occurring in ≥2% of patients receiving Terconazole Vaginal Cream in the trial. The therapy-related discontinuation rate was 2.0% for Terconazole Vaginal Cream. The adverse reaction most frequently causing discontinuation of Terconazole Vaginal Cream therapy was vulvovaginal itching (0.7%).

Table 1: Adverse Reactions Occurring in ≥2% of Patients Receiving Terconazole Vaginal Cream in a Randomized, Double-Blind Active Controlled Trial

 | Terconazole Vaginal Cream, 0.8%; n=231 (%) | Terazol®3; n=229 (%)
Headache | 49 (21) | 37(16)
Dysmenorrhea | 14 (6) | 5 (2)
Genital Burning and Itching | 12 (5) | 15-21 (6-9)
Abdominal Pain | 8 (3.4) | 2 (1)

Other adverse reactions reported in less than 2% of patients receiving Terconazole Vaginal Cream was fever (1%).

Photosensitivity reactions were observed in some normal volunteers following repeated dermal application of terconazole 2.0% (not an approved strength) and 0.8% creams under conditions of filtered artificial ultraviolet light. Photosensitivity reactions were not observed in U.S. and foreign clinical trials in patients who were treated with other terconazole formulations (i.e., terconazole suppositories or vaginal cream, 0.8%).

7 DRUG INTERACTIONS

Oral Contraceptives: There is no known interaction with the concomitant use of this product and oral contraceptives.

8 USE IN SPECIFIC POPULATIONS

8.1 Pregnancy

Risk Summary

There are no available data on Terconazole Vaginal Cream use in pregnant women to evaluate for a drug-associated risk of major birth defects, miscarriage, or adverse maternal or fetal outcomes. Available data from observational studies with terconazole use in pregnancy are insufficient to identify a drug-associated risk of major birth defects, miscarriage or adverse maternal or fetal outcomes.

In animal reproduction studies with oral terconazole, no adverse development effects were observed at clinically relevant systemic exposures (see Data).

The background risk of major birth defects and miscarriage for the indicated population is unknown. All pregnancies have a background risk of birth defect, loss, or other adverse outcomes. In the U.S. general population, the estimated background risk of major birth defects and miscarriage in clinically recognized pregnancies is 2% to 4% and 15% to 20%, respectively.

Data

Animal Data

There was no evidence of malformations when terconazole was administered orally in rats, or rabbits.

There was a delay in fetal ossification at an oral dose of 10 mg/kg/day in rats. Higher doses resulted in decreased litter size, decreased number of viable young and reduced fetal weight in rats. There was also a delay in ossification and an increase incidence of skeletal variants.

The dose of 10 mg/kg/day resulted in a mean peak plasma level of terconazole in pregnant rats of 0.176 mcg/mL which exceeds by 30 times the mean peak plasma level (0.006 mcg/mL) seen in normal subjects after intravaginal administration of terconazole vaginal cream 0.8%. This safety assessment does not account for possible exposure of the fetus through direct transfer to terconazole from the irritated vagina by diffusion across amniotic membranes.

8.2 Lactation

Risk Summary

There are no data on the presence of terconazole in human milk, the effect on the breast-fed infant or on milk production. The developmental and health benefits of breastfeeding should be considered along with the mother’s clinical need for Terconazole Vaginal Cream and any potential adverse effects on the breast-fed infant from Terconazole Vaginal Cream or from the underlying maternal condition.

8.4 Pediatric Use

The safety and effectiveness of Terconazole Vaginal Cream have not been established in female pediatric patients for the treatment of vulvovaginal candidiasis.

8.5 Geriatric Use

Clinical studies of Terconazole Vaginal Cream did not include sufficient numbers of subjects aged 65 and over to determine whether they respond differently from younger subjects.

10 OVERDOSAGE

Overdosage of terconazole in humans has not been reported to date.

11 DESCRIPTION

Terconazole Vaginal Cream, 0.8% is a white to off-white, water washable cream for intravaginal administration containing 0.8% of the antifungal agent terconazole, cis-1-[p[[2-(2,4-Dichlorophenyl)-2-(1H-1,2,4-triazol-1-ylmethyl)-1,3-dioxolan-4- yl]methoxy]phenyl]-4-isopropylpiperazine, compounded in a cream base consisting of butylated hydroxyanisole, cetyl alcohol, isopropyl myristate, polysorbate 60, polysorbate 80, propylene glycol, stearyl alcohol, and purified water. The structural formula of terconazole is as follows:

Terconazole, a triazole derivative, is a white to almost white powder with a molecular weight of 532.47. It is insoluble in water; sparingly soluble in ethanol; and soluble in butanol.

12 CLINICAL PHARMACOLOGY

12.1 Mechanism of Action

Terconazole is an antifungal agent [see Microbiology (12.4)].

12.3 Pharmacokinetics

Following intravaginal administration of Terconazole Vaginal Cream, 0.8% in adult females, absorption ranged from 5-8% in three hysterectomized subjects and 12-16% in two non-hysterectomized subjects with tubal ligations.

Following daily intravaginal administration of 0.8% terconazole 40 mg (0.8% cream x 5 g) for seven days to healthy female subjects, plasma concentrations were low and gradually rose to a daily peak (mean of 5.9 ng/mL or 0.006 mcg/mL) at 6.6 hours. Results from similar studies in female patients with vulvovaginal candidiasis indicate that the slow rate of absorption, the lack of accumulation, and the mean peak plasma concentration of terconazole was not different from that observed in healthy females. The absorption characteristics of terconazole vaginal cream, 0.8% in pregnant or non-pregnant patients with vulvovaginal candidiasis were also similar to those found in healthy subjects.

Following oral (30 mg) administration of ^14C-labelled terconazole, the mean half-life of elimination from the blood for the parent terconazole was 6.9 hours (range 4.0-11.3). Terconazole is extensively metabolized; the plasma AUC for terconazole compared to the AUC for total radioactivity was 0.6%. Total radioactivity was eliminated from the blood with a mean elimination half-life of 52.2 hours (range 44-60). Excretion of radioactivity was both by renal (32-56%) and fecal (47- 52%) routes.

In vitro, terconazole is highly protein bound (94.9%) and the degree of binding is independent of drug concentration.

12.4 Microbiology

Mechanism of Action

Terconazole inhibits the enzyme cytochrome P450 14α-demethylase which leads to inhibition of ergosterol synthesis, an essential component of the fungal cell membrane

Activity in vitro

Terconazole exhibits fungicidal activity in vitro against Candida albicans.

Drug Resistance

Studies showed no development of resistance to terconazole during successive passages of C. albicans. However, the clinical significance of such an effect is not known.

13 NONCLINICAL TOXICOLOGY

13.1 Carcinogenesis, Mutagenesis, Impairment of Fertility

Carcinogenesis

Studies to determine the carcinogenic potential of terconazole have not been performed.

Mutagenesis

Terconazole was not mutagenic when tested in vitro for induction of microbial point mutations (Ames test), or for inducing cellular transformation, or in vivo for chromosome breaks (micronucleus test) or dominant lethal mutations in mouse germ cells.

Impairment of Fertility

No impairment of fertility occurred when female rats were administered terconazole orally up to 40 mg/kg/day (about 10 times the recommended intravaginal human dose based on body surface area comparisons) for a three-month period.

14 CLINICAL STUDIES

The efficacy of Terconazole Vaginal Cream, 0.8% in the treatment of vulvovaginal candidiasis in adult women was evaluated in a multicenter, randomized, double-blind, controlled non-inferiority trial comparing Terconazole Vaginal Cream, 0.8% for 3 days (n=231) to another preparation of terconazole vaginal cream 0.8% active comparator for 3 days (n=229). The modified intent-to-treat population (randomized patients who received treatment and had a positive baseline culture for Candida) consisted of 140 Terconazole Vaginal Cream, 0.8% patients and 153 active comparator patients. Therapeutic cure defined as clinical and mycological cure was assessed at Visit 3 (Day 21-30). Table 2 shows the therapeutic, clinical and mycological cure rates in this trial. The therapeutic cure rate at Visit 3 was 67.1% for the terconazole group and 52.3% for the active comparator group (95% confidence interval about the 14.8% difference in therapeutic cure rate: 3.0% to 26.6%).

Table 2: Efficacy of Terconazole Vaginal Cream 0.8% for the Treatment of Vulvovaginal Candidiasis in a Randomized, Double-Blind Active Controlled Study*

Outcome | Terconazole Vaginal Cream 0.8%; n=140 (%) | Active Control; n=153 | Treatment Difference (%) [95% Confidence Interval]
 | % Cure | % Cure
Therapeutic Cure | 67.1 | 52.3 | 14.8 [3.0, 26.6]
Clinical Cure | 79.3 | 66.0 | 13.3 [2.5, 24.0]
Mycological Cure | 70.7 | 56.9 | 13.8 [2.2, 25.4]

* Modified intent-to-treat population

16 HOW SUPPLIED/STORAGE AND HANDLING

Terconazole Vaginal Cream 0.8% is supplied in a 20-gram tube with a measured dose applicator.

NDC 0168-0347-20

Store at 20°C to 25°C (68°F to 77°F), excursions permitted 15°C to 30°C (59°F to 86°F) [see USP Controlled Room Temperature].

17 PATIENT COUNSELING INFORMATION

Advise the patient to read the FDA-approved patient labeling (Patient Information and Instructions for Use).

Risk of Skin Irritation and Flu-like Symptoms

Advise the patient to discontinue Terconazole Vaginal Cream, 0.8 % and not to retreat if skin irritation, fever, chills or flu-like symptoms are reported during use.

Important Administration Instructions

Inform patients using Terconazole Vaginal Cream, 0.8% of the following important administration instructions:

- Terconazole Vaginal Cream, 0.8% is for intravaginal use only. Avoid contact with eyes and inside the nose and mouth.
- Terconazole Vaginal Cream, 0.8% should be used for three days as directed, even if you feel better quickly.
- Do not use this Terconazole Vaginal Cream for any disorder other than the one for which it was prescribed.
- Terconazole Vaginal Cream, 0.8% should be used once a day as directed.
- If your sexual partner has itching, redness or discomfort in the genital area, tell your partner to consult a physician and that you are being treated for a yeast infection.
- Terconazole Vaginal Cream, 0.8% can be used during a menstrual period but external pads should be used until the medication treatment has been completed. Tampons may absorb the medication and should not be used. You may wish to wear an absorbent panty liner while using Terconazole Vaginal Cream, 0.8%.
- Don’t scratch the vaginal area. Scratching can cause more irritation and spread the infection.
- Wash hands before and after applying Terconazole Vaginal Cream, 0.8%.

Inform patients who are prone to vaginal yeast infections of the following additional instructions:

- Dry the genital area thoroughly after showering, bathing, or swimming. Change out of a wet bathing suit or damp exercise clothes as soon as possible. A dry environment is less likely to encourage the growth of yeast.
- Wipe from front to rear (away from the vagina) after a bowel movement.
- Don’t douche unless the healthcare provider specifically tells you to do so. Douching may disturb the balance of normal bacterial flora and the pH of secretions.

The brands listed are the registered trademarks of their respective owners and are not trademarks of Fougera Pharmaceuticals Inc.

Manufactured by:

E. FOUGERA & CO.

A division of Fougera Pharmaceuticals Inc.

Melville, New York 11747

PATIENT INFORMATION

TERCONAZOLE VAGINAL CREAM (ter kon ah zol)

Important: For use in the vagina only. Terconazole vaginal cream is not for use in the mouth or eyes.

Read the Patient Information that comes with Terconazole vaginal cream before you start using it and each time you get a refill. There may be new information. This leaflet does not take the place of talking with your doctor about your medical condition or treatment.

What is Terconazole vaginal cream?

Terconazole vaginal cream is prescription medicine used to treat vaginal yeast infections caused by a fungus called Candida in adult females.

It is not known if Terconazole vaginal cream is safe or effective in female children.

Do not use Terconazole vaginal cream if you:

are allergic to terconazole or any of the other ingredients of the cream. See the end of this leaflet for a complete list of ingredients in Terconazole vaginal cream.

Before using Terconazole vaginal cream, tell your healthcare provider about all of your medical conditions, including if you:

- have had an allergic reaction to another antifungal medicine.
- are pregnant or plan to become pregnant. It is not known if Terconazole vaginal cream will harm your unborn baby.
- are breastfeeding or plan to breastfeed. It is not known if Terconazole vaginal cream passes into your breast milk.

Tell your healthcare provider about all the medicines that you take including prescription and non-prescription medicines, vitamins and herbal supplements. Certain types of medicines can increase the chance of getting vaginal infections.

How should I use Terconazole vaginal cream?

- Use Terconazole vaginal cream exactly as your healthcare provider tells you to use it.
- Use 1 full applicator of Terconazole vaginal cream in the vagina each night at bedtime for 3 days in a row.
- Terconazole vaginal cream is not for use in the mouth or eyes.
- Do not stop using Terconazole vaginal cream before your healthcare provider tells you to, even if you feel better very quickly. Your infection may not clear up completely.
- See the end of this leaflet for detailed Instructions for Use about how to use Terconazole vaginal cream correctly.
- Avoid scratching the affected area. Scratching may cause more irritation and spread the infection.
- If your sexual partner has itching, redness, or discomfort in the genital area, tell your partner to see their healthcare provider and tell their healthcare provider that you are being treated for a yeast infection.
- Terconazole vaginal cream can be used during a menstrual period. You should not use tampons because they absorb the medicine. Use external pads until treatment with Terconazole vaginal cream has been completed.
- Follow your healthcare provider’s instructions about how to reduce your chances of getting vaginal yeast infections.

What are possible side effects with Terconazole vaginal cream?

Terconazole vaginal cream may cause serious side effects, including skin irritation and flu-like symptoms. Stop using Terconazole vaginal cream and do not use Terconazole vaginal cream again if you get any of the following symptoms during treatment:

- skin irritation
- fever, chills, or flu-like symptoms

If you have any of the symptoms listed above, tell your healthcare provider. Your healthcare provider may tell you to stop using Terconazole vaginal cream and prescribe a different medicine to treat your fungal infection.

Common side effects of Terconazole vaginal cream include:

- headache
- painful menstrual periods
- genital itching and burning
- stomach pain

Tell your healthcare provider if you have any side effect that bothers you or that does not go away. These are not all the possible side effects of Terconazole vaginal cream. Ask your healthcare provider or pharmacist for more information.

Call your doctor for advice about side effects. You may report side effects to the FDA at 1-800-FDA-1088.

How should I store Terconazole vaginal cream?

- Store Terconazole vaginal cream at room temperature between 68°F to 77°F (20°C to 25°C).

Keep Terconazole vaginal cream and all medicines out of the reach of children.

General information about the safe and effective use of Terconazole vaginal cream

Medicines are sometimes prescribed for purposes other than those listed in Patient Information leaflet. Do not use Terconazole vaginal cream for a condition for which it was not prescribed. Do not give Terconazole vaginal cream to other people, even if they have the same symptoms you have. It may harm them.

You can ask your pharmacist or healthcare provider for information about Terconazole vaginal cream that is written for health professionals.

What are the ingredients in Terconazole vaginal cream?

Active ingredient: terconazole 0.8%

Inactive ingredients: butylated hydroxyanisole, cetyl alcohol, isopropyl myristate, polysorbate 60, polysorbate 80, propylene glycol, stearyl alcohol, and purified water.

Manufactured by:

E. FOUGERA & CO.

A division of Fougera Pharmaceuticals Inc.

Melville, New York 11747

For more information, call 1-800-645-9833.

This Patient Information has been approved by the U.S. Food and Drug Administration Revised: September 2025

INSTRUCTIONS FOR USE

TERCONAZOLE VAGINAL CREAM (ter kon ah zol)

For vaginal use only. Do not put Terconazole vaginal cream in your eyes or mouth.

Be sure to read, understand, and follow the instructions below for how to use Terconazole vaginal cream, correctly.

Important Information

- Use Terconazole vaginal cream exactly as your healthcare provider tells you to use it.
- Use1 full applicator of terconazole vaginal cream in the vagina each night at bedtime for 3 days in a row.
- Do not stop using Terconazole vaginal cream before your healthcare provider tells you to, even if you feel better very quickly. Your infection may not clear up completely.
- If you have questions or if your vaginal symptoms do not go away, contact your healthcare provider.

How should I store terconazole vaginal cream?

- Store Terconazole vaginal cream at room temperature between 68°F to 77°F (20°C to 25°C).

Keep Terconazole vaginal cream and all medicines out of the reach of children.

Step 1. Gather your supplies. (Figure 1)

- 1 Terconazole vaginal cream tube
- 1 empty reusable applicator, to fill and give the dose of medicine.

Step 2. Wash your hands.

Step 3. Prepare the Applicator:

- Remove the cap from the Terconazole vaginal cream tube.
- Use the pointed tip on the top of the cap to puncture the seal on the tube. (See Figure 2)
- Screw the applicator onto the tube.
- Squeeze the tube from the bottom and fill the applicator until the plunger stops. (See Figure 3)
- Unscrew the applicator from the tube.

Step 4. Insert the Terconazole vaginal cream:

- Lie on your back with knees drawn up toward your chest.
- Holding the applicator by the ribbed end of the barrel, insert the filled applicator into the vagina as far as it will comfortably go. (See Figure 4)
- Slowly press the plunger of the applicator to release the cream into the vagina.
- Remove the applicator from the vagina. Wash the applicator.

Step 5. Wash the Applicator after Use

- Wash the applicator after each use.
- Pull the plunger out of the barrel. (See Figure 5)
- Wash the applicator pieces with lukewarm, soapy water and then dry them very well.
- Put the dry applicator pieces back together by gently pushing the plunger into the barrel as far as it will go.

Step 6. Wash your hands well after you finish washing and drying the applicator.

Step 7. Repeat Steps 1 through Step 6 until you finish your course of treatment.

Step 8. When you have finished your treatment, throw away (dispose of) the used applicator and tube in your household trash.

Manufactured by:

E. FOUGERA & CO.

A division of Fougera Pharmaceuticals Inc.

Melville, New York 11747

The brands listed are the registered trademarks of their respective owners and are not trademarks of Fougera Pharmaceuticals Inc.

This Instructions for Use has been approved by the U.S Food and Drug Administration Revised: 09/2025

PACKAGE/LABEL PRINCIPAL DISPLAY PANEL

NDC 0168-0347-20 Rx Only

Terconazole Vaginal Cream 0.8%

Tube and Applicator

NET WT 20 grams

Fougera